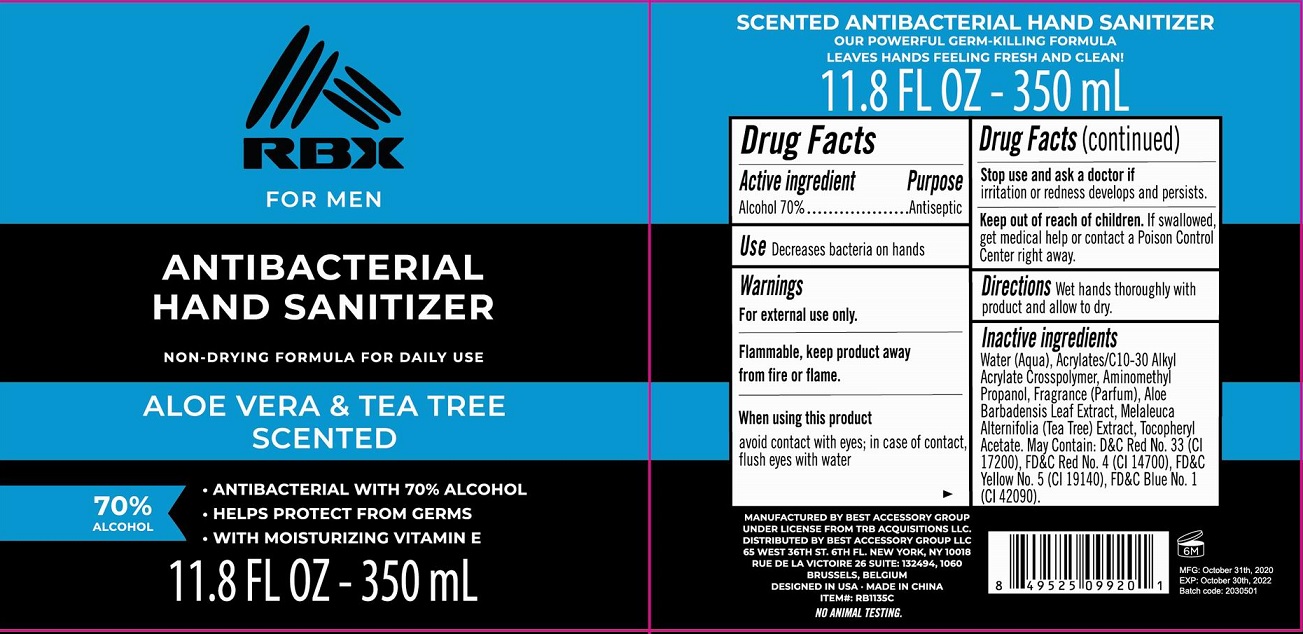 DRUG LABEL: RBX For Men Antibacterial Hand Sanitizer Aloe Vera and Tea Tree Scented
NDC: 56136-520 | Form: LIQUID
Manufacturer: Ganzhou Olivee Cosmetic Co., Ltd.
Category: otc | Type: HUMAN OTC DRUG LABEL
Date: 20210106

ACTIVE INGREDIENTS: ALCOHOL 70 mL/100 mL
INACTIVE INGREDIENTS: WATER; CARBOMER COPOLYMER TYPE A; AMINOMETHYLPROPANOL; TEA TREE OIL; ALOE VERA LEAF; .ALPHA.-TOCOPHEROL ACETATE, D-; FD&C RED NO. 3; FD&C RED NO. 4; FD&C YELLOW NO. 5; FD&C BLUE NO. 1; D&C RED NO. 33

Active ingredient

Alcohol 70%

Purpose

Antiseptic

Use

Decrease bacteria on hands

Warnings

For external use only.

When using this product

avoid contact with eyes; in case of contact, flush eyes with water.

Stop use and ask a doctor if

- irritation and redness develops and persists.

Keep out of reach of children.

If swallowed, get medical help or contact a Poison Control Center right away.

Directions

Apply onto wet hands working into a lather. Rinse thorougly.

Inactive ingredients

Water (Aqua), Cocamidopropyl Betaine, Cocamidopropylamine Oxide, Hydroxethylcellulose, Fragrance (Parfum), Phenoxyethanol, Bezyl Alcohol, PEG-150 Distearate, Sodium Chloride, Glycerin, Citric Acid, Aloe Barbadensis Leaf Etract, Melaleuca alternifolia (Tea Tree) Extract, Tocopheryl Acetate. May contain: FD&C Red No. 4 (C.I. 14700), FD&C Yellow No. 5 (C.I. 19140), D&C Red No. 33 (Cl 17200), FD&C Blue No. 1 (Cl 42090).